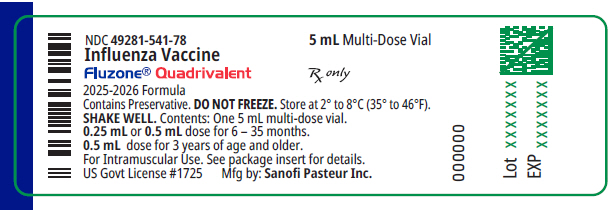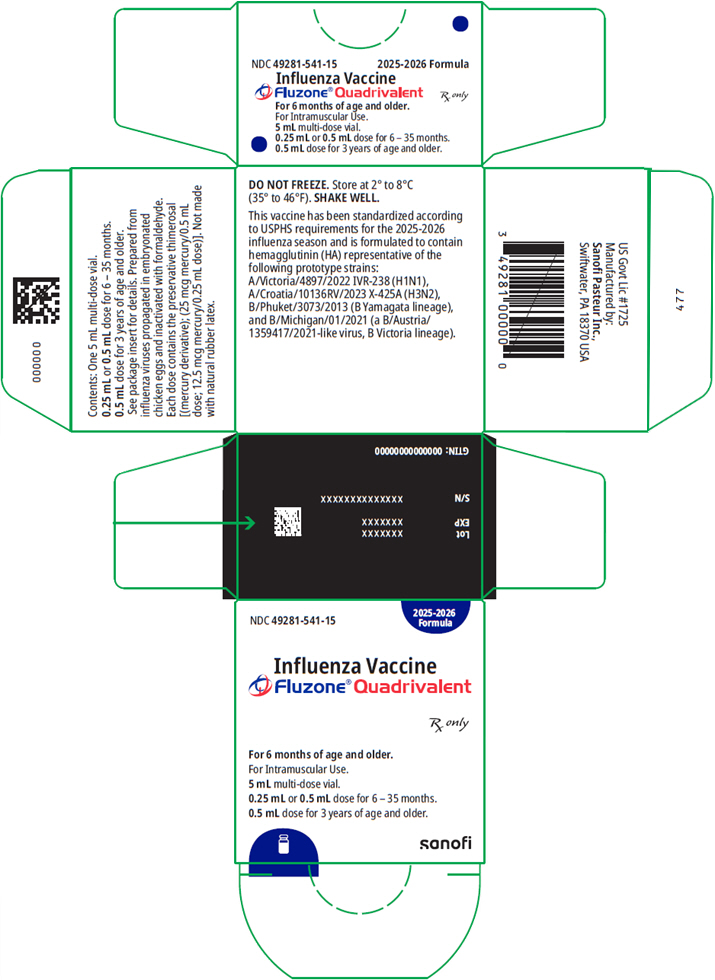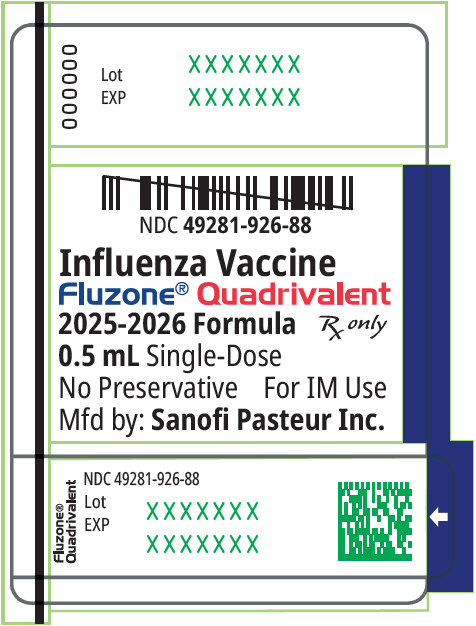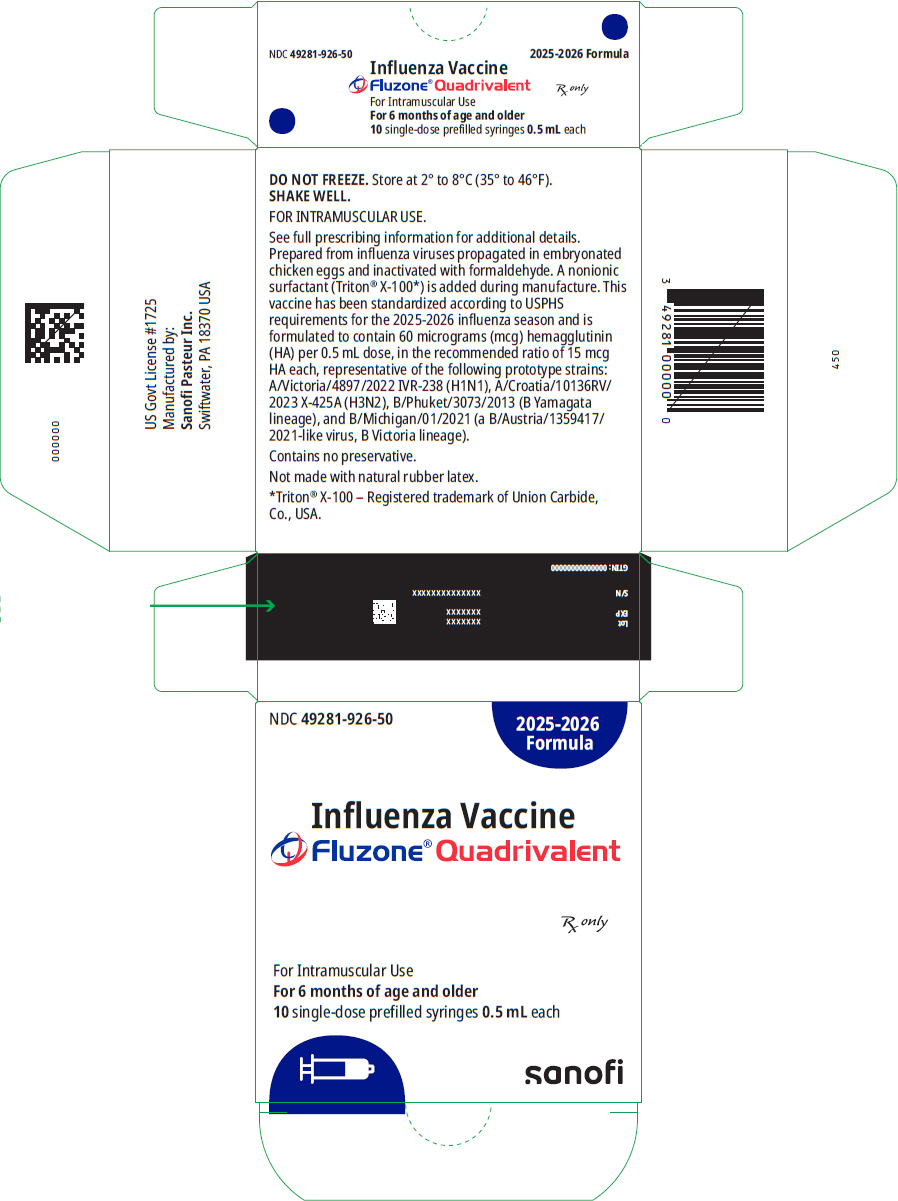 DRUG LABEL: Fluzone Quadrivalent Northern Hemisphere
NDC: 49281-541 | Form: INJECTION, SUSPENSION
Manufacturer: Sanofi Pasteur Inc.
Category: other | Type: VACCINE LABEL
Date: 20250711

ACTIVE INGREDIENTS: INFLUENZA A VIRUS A/VICTORIA/4897/2022 IVR-238 (H1N1) ANTIGEN (FORMALDEHYDE INACTIVATED) 15 ug/0.5 mL; INFLUENZA A VIRUS A/CROATIA/10136RV/2023 X-425A (H3N2) ANTIGEN (FORMALDEHYDE INACTIVATED) 15 ug/0.5 mL; INFLUENZA B VIRUS B/PHUKET/3073/2013 ANTIGEN (FORMALDEHYDE INACTIVATED) 15 ug/0.5 mL; INFLUENZA B VIRUS B/MICHIGAN/01/2021 ANTIGEN (FORMALDEHYDE INACTIVATED) 15 ug/0.5 mL
INACTIVE INGREDIENTS: SODIUM PHOSPHATE, MONOBASIC, ANHYDROUS; SODIUM PHOSPHATE, DIBASIC, ANHYDROUS; FORMALDEHYDE; THIMEROSAL; OCTOXYNOL-9; WATER

HIGHLIGHTS OF PRESCRIBING INFORMATION

These highlights do not include all the information needed to use Fluzone® Quadrivalent safely and effectively. See full prescribing information for Fluzone Quadrivalent.
Fluzone Quadrivalent (Influenza Vaccine) injectable suspension, for intramuscular use
2025-2026 Formula
Initial U.S. Approval: 2013

1 INDICATIONS AND USAGE

Fluzone Quadrivalent is a vaccine indicated for active immunization for the prevention of disease caused by influenza A subtype viruses and type B viruses contained in the vaccine. (1)

Fluzone Quadrivalent is approved for use in persons 6 months of age and older. (1)

2 DOSAGE AND ADMINISTRATION

- For intramuscular use (2)

Age | Vaccination Status | Dose | Schedule
6 months through 35 months | Not previously vaccinated with influenza vaccine or unknown vaccination history | Two doses, either 0.25 mL or 0.5 mL [The schedule can be completed as two 0.25-mL doses ≥4 weeks apart, two 0.5-mL doses ≥4 weeks apart, or any combination of 2 doses (either 0.25 mL or 0.5 mL) administered ≥4 weeks apart.] | Administer at least 4 weeks apart
6 months through 35 months | Previously vaccinated with influenza vaccine | One or two doses [To determine if 1 or 2 doses are required, refer to Advisory Committee on Immunization Practices annual recommendations on prevention and control of influenza with vaccines.] , either 0.25 mL or 0.5 mL | If two doses, administer at least 4 weeks apart
36 months through 8 years | Not previously vaccinated with influenza vaccine or unknown vaccination history | Two 0.5 mL doses | Administer at least 4 weeks apart
36 months through 8 years | Previously vaccinated with influenza vaccine | One or two 0.5 mL doses | If two doses, administer at least 4 weeks apart
9 years and older | - | One 0.5 mL dose | -
"-" Indicates information is not applicable

3 DOSAGE FORMS AND STRENGTHS

Fluzone Quadrivalent is an injectable suspension.

For individuals 6 months through 35 months, a single-dose is 0.25 mL or 0.5 mL.

For individuals 36 months and older, a single-dose is 0.5 mL. (3)

4 CONTRAINDICATIONS

Do not administer Fluzone Quadrivalent to anyone with a history of severe allergic reaction (e.g., anaphylaxis) to any component of the vaccine, including egg protein, or after previous dose of any influenza vaccine. (4,11)

5 WARNINGS AND PRECAUTIONS

If Guillain-Barré syndrome (GBS) has occurred within 6 weeks following previous influenza vaccination, the decision to give Fluzone Quadrivalent should be based on careful consideration of the potential benefits and risks. (5.1)

6 ADVERSE REACTIONS

- In children 6 months through 35 months of age, the most common (≥10%) injection-site adverse reactions were pain (57%) or tenderness (47%–54%), erythema (23%–37%), and swelling (13%–22%); the most common solicited systemic adverse reactions were irritability (47%–54%), abnormal crying (33%–41%), malaise (38%), drowsiness (31%–38%), appetite loss (27%–32%), myalgia (27%), vomiting (10%–15%), and fever (11%–14%). (6.1)
- In children 3 years through 8 years of age, the most common (≥10%) injection-site adverse reactions were pain (67%), erythema (34%), and swelling (25%); the most common solicited systemic adverse reactions were myalgia (39%), malaise (32%), and headache (23%). (6.1)
- In adults 18 years and older, the most common (≥10%) injection-site adverse reaction was pain (47%); the most common solicited systemic adverse reactions were myalgia (24%), headache (16%), and malaise (11%). (6.1)
- In adults 65 years of age and older, the most common (≥10%) injection-site adverse reaction was pain (33%); the most common solicited systemic adverse reactions were myalgia (18%), headache (13%), and malaise (11%). (6.1)

To report SUSPECTED ADVERSE REACTIONS, contact Sanofi Pasteur Inc., at 1-800-822-2463 (1-800-VACCINE) or VAERS at 1-800-822-7967 or www.vaers.hhs.gov.

8 USE IN SPECIFIC POPULATIONS

- Antibody responses to Fluzone Quadrivalent are lower in persons ≥65 years of age than in younger adults. (8.5)

FULL PRESCRIBING INFORMATION

1 INDICATIONS AND USAGE

Fluzone® Quadrivalent is a vaccine indicated for active immunization for the prevention of disease caused by influenza A subtype viruses and type B viruses contained in the vaccine.

Fluzone Quadrivalent is approved for use in persons 6 months of age and older.

2 DOSAGE AND ADMINISTRATION

For intramuscular use

2.1 Dose and Schedule

The dose and schedule for Fluzone Quadrivalent are presented in Table 1.

Table 1: Dose and Schedule for Fluzone Quadrivalent
Age | Vaccination Status | Dose | Schedule
6 months through 35 months | Not previously vaccinated with influenza vaccine or unknown vaccination history | Two doses, either 0.25 mL or 0.5 mL [The schedule can be completed as two 0.25-mL doses ≥4 weeks apart, two 0.5-mL doses ≥4 weeks apart, or any combination of 2 doses (either 0.25 mL or 0.5 mL) administered ≥4 weeks apart] | Administer at least 4 weeks apart
6 months through 35 months | Previously vaccinated with influenza vaccine | One or two doses [To determine if 1 or 2 doses are required, refer to Advisory Committee on Immunization Practices annual recommendations on prevention and control of influenza with vaccines] , either 0.25 mL or 0.5 mL | If two doses, administer at least 4 weeks apart
36 months through 8 years | Not previously vaccinated with influenza vaccine or unknown vaccination history | Two 0.5 mL doses | Administer at least 4 weeks apart
36 months through 8 years | Previously vaccinated with influenza vaccine | One or two 0.5 mL doses | If two doses, administer at least 4 weeks apart
9 years and older | - | One 0.5 mL dose | -
"-" Indicates information is not applicable

2.2 Administration

Fluzone Quadrivalent is clear and slightly opalescent in color. Parenteral drug products should be inspected visually for particulate matter and/or discoloration prior to administration, whenever solution and container permit. If any of these defects or conditions exist, Fluzone Quadrivalent should not be administered.

Before administering a dose of vaccine, shake the prefilled syringe or multi-dose vial. A maximum of ten doses can be withdrawn from the multi-dose vial.

Administer each dose intramuscularly.

3 DOSAGE FORMS AND STRENGTHS

Fluzone Quadrivalent is an injectable suspension. For individuals 6 months through 35 months, a single dose is 0.25 mL or 0.5 mL.

For individuals 36 months and older, a single dose is 0.5 mL.

4 CONTRAINDICATIONS

Do not administer Fluzone Quadrivalent to anyone with a history of a severe allergic reaction (e.g., anaphylaxis) to any component of the vaccine [see Description (11)], including egg protein, or to a previous dose of any influenza vaccine.

5 WARNINGS AND PRECAUTIONS

5.1 Guillain Barré Syndrome

If Guillain Barré Syndrome (GBS) has occurred within 6 weeks following previous influenza vaccination, the decision to give Fluzone Quadrivalent should be based on careful consideration of the potential benefits and risks.

The 1976 swine influenza vaccine was associated with an elevated risk of GBS. Evidence for a causal relation of GBS with other influenza vaccines is inconclusive; if an excess risk exists, it is probably slightly more than 1 additional case per 1 million persons vaccinated. (1)

5.2 Preventing and Managing Allergic Reactions

Appropriate medical treatment must be immediately available to manage potential anaphylactic reactions following administration of Fluzone Quadrivalent.

5.3 Altered Immunocompetence

If Fluzone Quadrivalent is administered to immunocompromised persons, including those receiving immunosuppressive therapy, the expected immune response may not be obtained.

5.4 Limitations of Vaccine Effectiveness

Vaccination with Fluzone Quadrivalent may not protect all recipients.

5.5 Syncope

Syncope (fainting) has been reported following vaccination with Fluzone Quadrivalent. Procedures should be in place to avoid injury from fainting.

6 ADVERSE REACTIONS

In children 6 months through 35 months of age, the most common (≥10%) injection-site adverse reactions were pain (57%) or tenderness (47%– 54%), erythema (23%–37%), and swelling (13%–22%); the most common solicited systemic adverse reactions were irritability (47%– 54%), abnormal crying (33%–41%), malaise (38%), drowsiness (31%– 38%), appetite loss (27%–32%), myalgia (27%), vomiting (10%–15%), and fever (11%–14%).

In children 3 years through 8 years of age, the most common (≥10%) injection-site adverse reactions were pain (67%), erythema (34%), and swelling (25%); the most common solicited systemic adverse reactions were myalgia (39%), malaise (32%), and headache (23%).

In adults 18 years and older, the most common (≥10%) injection-site adverse reaction was pain (47%); the most common solicited systemic adverse reactions were myalgia (24%), headache (16%), and malaise (11%).

In adults 65 years of age and older, the most common (≥10%) injection-site adverse reaction was pain (33%); the most common solicited systemic adverse reactions were myalgia (18%), headache (13%), and malaise (11%).

6.1 Clinical Trials Experience

Because clinical trials are conducted under widely varying conditions, adverse event rates observed in the clinical trials of a vaccine cannot be directly compared to rates in the clinical trial(s) of another vaccine and may not reflect the rates observed in practice.

Children 6 Months Through 8 Years of Age

Study 1 (NCT01240746) was a single-blind, randomized, active-controlled multi-center safety and immunogenicity study conducted in the US. In this study, children 6 months through 35 months of age received one or two 0.25 mL doses of either Fluzone Quadrivalent or one of two formulations of a comparator trivalent influenza vaccine (TIV-1 or TIV-2), and children 3 years through 8 years of age received one or two 0.5 mL doses of either Fluzone Quadrivalent, TIV-1, or TIV-2. Each of the trivalent formulations contained an influenza type B virus that corresponded to one of the two type B viruses in Fluzone Quadrivalent (a type B virus of the Victoria lineage or a type B virus of the Yamagata lineage). For participants who received two doses, the doses were administered approximately 4 weeks apart. The safety analysis set included 1841 children 6 months through 35 months of age and 2506 children 3 years through 8 years of age. Among participants 6 months through 8 years of age in the three vaccine groups combined, 49.3% were female (Fluzone Quadrivalent, 49.2%; TIV-1, 49.8%; TIV-2, 49.4%), 58.4% Caucasian (Fluzone Quadrivalent, 58.4%; TIV-1, 58.9%; TIV-2, 57.8%), 20.2% Black (Fluzone Quadrivalent, 20.5%; TIV-1, 19.9%; TIV-2, 19.1%), 14.1% Hispanic (Fluzone Quadrivalent, 14.3%; TIV-1, 13.2%; TIV-2, 14.7%), and 7.3% were of other racial/ethnic groups (Fluzone Quadrivalent, 6.8%; TIV-1, 8.0%; TIV-2, 8.5%). Table 2 and Table 3 summarize solicited injection-site and systemic adverse reactions reported within 7 days post-vaccination via diary cards. Participants were monitored for unsolicited adverse events for 28 days after each dose and serious adverse events (SAEs) during the 6 months following the last dose.

Table 2: Percentage of Solicited Injection-site and Systemic Adverse Reactions Within 7 Days After Vaccination in Children 6 Months Through 35 Months of Age (Safety Analysis Set) [The safety analysis set includes all persons who received at least one dose of study vaccine] (Study 1 [NCT01240746])
 | Fluzone Quadrivalent [Fluzone Quadrivalent (0.25 mL) containing A/California/07/2009 (H1N1), A/Victoria/210/2009 (H3N2), B/Brisbane/60/2008 (Victoria lineage), and B/Florida/04/2006 (Yamagata lineage)] , [Participants received 1 or 2 doses according to ACIP recommendations] (N [N is the number of participants in the safety analysis set] =1223) |  |  | TIV-1, [2010-2011 Fluzone TIV (0.25 mL) containing A/California/07/2009 (H1N1), A/Victoria/210/2009 (H3N2), and B/Brisbane/60/2008 (Victoria lineage), licensed] (B Victoria) (N=310) |  |  | TIV-2, [Investigational TIV (0.25 mL) containing A/California/07/2009 (H1N1), A/Victoria/210/2009 (H3N2), and B/Florida/04/2006 (Yamagata lineage), non-licensed] (B Yamagata) (N=308)
 | Any (%) | Grade 2 [Grade 2 - Injection-site pain: sufficiently discomforting to interfere with normal behavior or activities; Injection-site tenderness: cries and protests when injection-site is touched; Injection-site erythema, Injection-site swelling: ≥2.5 cm to <5 cm; Fever: >101.3°F to ≤103.1°F (6 months through 23 months); ≥101.2°F to ≤102.0°F (24 months through 35 months); Malaise, Myalgia, and Headache: some interference with activity; Irritability: requiring increased attention; Crying abnormal: 1 to 3 hours; Drowsiness: not interested in surroundings or did not wake up for a feed/meal; Appetite loss: missed 1 or 2 feeds/meals completely; Vomiting: 2 to 5 episodes per 24 hours] (%) | Grade 3 [Grade 3 - Injection-site pain: incapacitating, unable to perform usual activities; Injection-site tenderness: cries when injected limb is moved, or the movement of the injected limb is reduced; Injection-site erythema, Injection-site swelling: ≥5 cm; Fever: >103.1°F (6 months through 23 months); ≥102.1°F (24 months through 35 months); Malaise, Myalgia, and Headache: Significant; prevents daily activity; Irritability: inconsolable; Crying abnormal: >3 hours; Drowsiness: sleeping most of the time or difficult to wake up; Appetite loss: refuses ≥3 feeds/meals or refuses most feeds/meals; Vomiting: ≥6 episodes per 24 hours or requiring parenteral hydration] (%) | Any (%) | Grade 2 (%) | Grade 3 (%) | Any (%) | Grade 2 (%) | Grade 3 (%)
Injection-site adverse reactions
Pain [Assessed in children 24 months through 35 months of age] | 57.0 | 10.2 | 1.0 | 52.3 | 11.5 | 0.8 | 50.3 | 5.4 | 2.7
Tenderness [Assessed in children 6 months through 23 months of age] | 54.1 | 11.3 | 1.9 | 48.4 | 8.2 | 1.9 | 49.7 | 10.3 | 0.0
Erythema | 37.3 | 1.5 | 0.2 | 32.9 | 1.0 | 0.0 | 33.3 | 1.0 | 0.0
Swelling | 21.6 | 0.8 | 0.2 | 19.7 | 1.0 | 0.0 | 17.3 | 0.0 | 0.0
Systemic adverse reactions
Fever (≥100.4°F) [Fever measured by any route] | 14.3 | 5.5 | 2.1 | 16.0 | 6.6 | 1.7 | 13.0 | 4.1 | 2.0
Malaise | 38.1 | 14.5 | 4.6 | 35.2 | 14.8 | 4.7 | 32.4 | 12.8 | 6.8
Myalgia | 26.7 | 6.6 | 1.9 | 26.6 | 9.4 | 1.6 | 25.0 | 6.8 | 2.7
Headache | 8.9 | 2.5 | 0.6 | 9.4 | 3.9 | 0.0 | 12.2 | 4.7 | 0.0
Irritability | 54.0 | 26.4 | 3.2 | 52.8 | 20.1 | 3.1 | 53.5 | 22.9 | 2.8
Crying abnormal | 41.2 | 12.3 | 3.3 | 36.5 | 8.2 | 1.9 | 29.9 | 10.4 | 2.1
Drowsiness | 37.7 | 8.4 | 1.3 | 32.1 | 3.8 | 0.6 | 31.9 | 5.6 | 0.7
Appetite loss | 32.3 | 9.1 | 1.8 | 33.3 | 5.7 | 1.9 | 25.0 | 8.3 | 0.7
Vomiting | 14.8 | 6.2 | 1.0 | 11.3 | 4.4 | 0.6 | 13.9 | 6.3 | 0.0

Table 3: Percentage of Solicited Injection-site and Systemic Adverse Reactions Within 7 Days After Vaccination in Children 3 Years Through 8 Years of Age (Safety Analysis Set) [The safety analysis set includes all persons who received at least one dose of study vaccine] (Study 1 [NCT01240746])
 | Fluzone Quadrivalent [Fluzone Quadrivalent containing A/California/07/2009 (H1N1), A/Victoria/210/2009 (H3N2), B/Brisbane/60/2008 (Victoria lineage), and B/Florida/04/2006 (Yamagata lineage)] (N [N is the number of participants in the safety analysis set] =1669) |  |  | TIV-1 [2010-2011 Fluzone TIV containing A/California/07/2009 (H1N1), A/Victoria/210/2009 (H3N2), and B/Brisbane/60/2008 (Victoria lineage), licensed] (B Victoria) (N=424) |  |  | TIV-2 [Investigational TIV containing A/California/07/2009 (H1N1), A/Victoria/210/2009 (H3N2), and B/Florida/04/2006 (Yamagata lineage), non-licensed] (B Yamagata) (N=413)
 | Any (%) | Grade 2 [Grade 2 - Injection-site pain: sufficiently discomforting to interfere with normal behavior or activities; Injection-site erythema, Injection-site swelling: ≥2.5 cm to <5 cm; Fever: ≥101.2°F to ≤102.0°F; Headache, Malaise, and Myalgia: some interference with activity] (%) | Grade 3 [Grade 3 - Injection-site pain: incapacitating, unable to perform usual activities; Injection-site erythema, Injection-site swelling: ≥5 cm; Fever: ≥102.1°F; Headache, Malaise, and Myalgia: Significant; prevents daily activity] (%) | Any (%) | Grade 2 (%) | Grade 3 (%) | Any (%) | Grade 2 (%) | Grade 3 (%)
Injection-site adverse reactions
Pain | 66.6 | 15.8 | 2.1 | 64.6 | 9.5 | 2.0 | 63.8 | 11.6 | 2.8
Erythema | 34.1 | 2.9 | 1.8 | 36.8 | 3.4 | 1.2 | 35.2 | 2.5 | 1.8
Swelling | 24.8 | 2.8 | 1.4 | 25.4 | 1.5 | 1.2 | 25.9 | 2.5 | 1.8
Systemic adverse reactions
Fever (≥100.4°F) [Fever measured by any route] | 7.0 | 2.1 | 2.1 | 7.1 | 2.2 | 1.2 | 7.6 | 2.8 | 0.8
Headache | 23.1 | 6.8 | 2.2 | 21.2 | 5.1 | 2.7 | 24.4 | 7.5 | 2.0
Malaise | 31.9 | 11.2 | 5.5 | 32.8 | 11.4 | 5.6 | 33.4 | 10.8 | 5.0
Myalgia | 38.6 | 12.2 | 3.3 | 34.1 | 9.0 | 2.7 | 38.4 | 11.1 | 2.8

Among children 6 months through 8 years of age, unsolicited non-serious adverse events were reported in 1360 (47.0%) recipients in the Fluzone Quadrivalent group, 352 (48.0%) recipients in the TIV-1 group, and 346 (48.0%) recipients in the TIV-2 group. The most commonly reported unsolicited non-serious adverse events were cough, vomiting, and pyrexia. During the 28 days following vaccination, a total of 16 (0.6%) recipients in the Fluzone Quadrivalent group, 4 (0.5%) recipients in the TIV-1 group, and 4 (0.6%) recipients in the TIV-2 group, experienced at least one SAE. Throughout the study period, a total of 41 (1.4%) recipients in the Fluzone Quadrivalent group, 7 (1.0%) recipients in the TIV-1 group, and 14 (1.9%) recipients in the TIV-2 group, experienced at least one SAE. Three SAEs were considered to be possibly related to vaccination: croup in a Fluzone Quadrivalent recipient and 2 episodes of febrile seizure, 1 each in a TIV-1 recipient and a TIV-2 recipient.

0.5-mL Dose of Fluzone Quadrivalent in Children 6 Months through 35 Months of Age

Study 2 (NCT02915302) was a randomized, observer-blinded, 2-arm, multi-center safety and immunogenicity study conducted in the US. In this study, 1950 children 6 months through 35 months of age were randomly assigned to receive Fluzone Quadrivalent administered in either a volume of 0.25 mL (Group 1) or 0.5 mL (Group 2). For participants recommended to receive two doses of influenza vaccine as per Advisory Committee on Immunization Practices guidance, the same dose was administered 4 weeks after the first. The safety analysis set included 1941 participants who received at least 1 dose of study vaccine. Of these participants, 49.7% were female, 74.3% were Caucasian, 19.2% were Black, 6.5% were of other racial groups, and 22.0% were Hispanic/Latino.

Table 4 summarizes solicited injection-site and systemic adverse reactions reported within 7 days post-vaccination via diary cards for the 0.25 mL and 0.5 mL volumes of Fluzone Quadrivalent in children 6 months through 35 months of age.

Table 4: Percentage of Solicited Injection-site and Systemic Adverse Reactions Within 7 Days After Vaccination in Children 6 Months Through 35 Months of Age (Safety Analysis Set) [The safety analysis set includes all persons who received at least one dose of study vaccine] (Study 2 [NCT02915302])
 | Fluzone Quadrivalent 0.25 mL [Participants received 1 or 2 doses according to ACIP recommendations] (N [N is the number of participants in the safety analysis set] =949) |  | Fluzone Quadrivalent 0.5 mL (N=992)
 | Any (%) | Grade 3 [Grade 3 - Injection-site tenderness: Cries when injected limb is moved, or the movement of the injected limb is reduced; Injection-site redness, Injection-site swelling: ≥50 mm; Irritability: inconsolable; Abnormal Crying: >3 hours; Drowsiness: sleeping most of the time or difficult to wake up; Loss of Appetite: refuses ≥3 feeds/meals or refuses most feeds/meals; Fever: >103.1°F; Vomiting: ≥6 episodes per 24 hours or requiring parenteral hydration] (%) | Any (%) | Grade 3 (%)
Injection-site adverse reactions
Tenderness | 47.3 | 1.7 | 50.4 | 1.2
Redness | 23.1 | 0.0 | 24.3 | 0.2
Swelling | 12.9 | 0.1 | 14.7 | 0.0
Systemic adverse reactions
Irritability | 47.4 | 3.6 | 48.6 | 4.0
Abnormal Crying | 33.3 | 3.1 | 34.1 | 2.6
Drowsiness | 31.9 | 2.1 | 31.3 | 1.6
Loss of Appetite | 27.3 | 1.4 | 28.3 | 2.2
Fever (≥100.4°F) [Fever measured by any route] | 11.3 | 0.6 | 12.2 | 1.2
Vomiting | 10.0 | 0.4 | 10.2 | 0.5

The difference in fever rate (Group 2 minus Group 1) was 0.84% (95% CI: -2.13%; 3.80%), meeting the prespecified non-inferiority criterion (upper limit of the 2-sided 95% CI of the difference in fever rates <5%). Participants were monitored for unsolicited adverse events and SAEs during the 28 days following vaccination. Unsolicited non-serious adverse events were reported in 417 (44%) participants in Group 1 and 394 (40%) participants in Group 2. The most commonly reported unsolicited non-serious adverse events in both groups were cough and rhinorrhea. Ten SAEs were reported during the 28-day follow-up period: 5 (0.5%) in Group 1 and 5 (0.5%) in Group 2.

Adults

In Study 3 (NCT00988143), a multi-centered randomized, open-label trial conducted in the US, adults 18 years of age and older received one dose of either Fluzone Quadrivalent or one of two formulations of comparator trivalent influenza vaccine (TIV-1 or TIV-2). Each of the trivalent formulations contained an influenza type B virus that corresponded to one of the two type B viruses in Fluzone Quadrivalent (a type B virus of the Victoria lineage or a type B virus of the Yamagata lineage). The safety analysis set included 570 recipients, half aged 18-60 years and half aged 61 years or older. Among participants in the three vaccine groups combined, 67.2% were female (Fluzone Quadrivalent, 68.4%; TIV-1, 67.9%; TIV-2, 65.3%), 88.4% Caucasian (Fluzone Quadrivalent, 91.1%; TIV-1, 86.8%; TIV-2, 87.4%), 9.6% Black (Fluzone Quadrivalent, 6.8%; TIV-1, 12.1%; TIV-2, 10.0%), 0.4% Hispanic (Fluzone Quadrivalent, 0.0%; TIV-1, 0.5%; TIV-2, 0.5%), and 1.7% were of other racial/ethnic groups (Fluzone Quadrivalent, 2.1%; TIV-1, 0.5%; TIV-2, 2.2%). Table 5 summarizes solicited injection-site and systemic adverse reactions reported within 3 days post-vaccination via diary cards. Participants were monitored for unsolicited adverse events and SAEs during the 21 days following vaccination.

Table 5: Percentage of Solicited Injection-site and Systemic Adverse Reactions Within 3 Days After Vaccination in Adults 18 Years of Age and Older (Safety Analysis Set) [The safety analysis set includes all persons who received study vaccine] (Study 3 [NCT00988143])
 | Fluzone Quadrivalent [Fluzone Quadrivalent containing A/California/07/2009 (H1N1), A/Victoria/210/2009 (H3N2), B/Brisbane/60/2008 (Victoria lineage), and B/Florida/04/2006 (Yamagata lineage)] (N [N is the number of participants in the safety analysis set] =190) |  |  | TIV-1 [2009-2010 Fluzone TIV containing A/Brisbane/59/2007 (H1N1), A/Uruguay/716/2007 (H3N2), and B/Brisbane/60/2008 (Victoria lineage), licensed] (B Victoria) (N=190) |  |  | TIV-2 [2008-2009 Fluzone TIV containing A/Brisbane/59/2007 (H1N1), A/Uruguay/716/2007 (H3N2), and B/Florida/04/2006 (Yamagata lineage), licensed] (B Yamagata) (N=190)
 | Any (%) | Grade 2 [Grade 2 - Injection-site pain: Some interference with activity; Injection-site erythema, Injection-site swelling, Injection-site induration, and Injection-site ecchymosis: ≥5.1 to ≤10 cm; Fever: ≥101.2°F to ≤102.0°F; Myalgia, Headache, Malaise, and Shivering: some interference with activity] (%) | Grade 3 [Grade 3 - Injection-site pain: Significant; prevents daily activity; Injection-site erythema, Injection-site swelling, Injection-site induration, and Injection-site ecchymosis: >10 cm; Fever: ≥102.1°F; Myalgia, Headache, Malaise, and Shivering: Significant; prevents daily activity] (%) | Any (%) | Grade 2 (%) | Grade 3 (%) | Any (%) | Grade 2 (%) | Grade 3 (%)
Injection-site adverse reactions
Pain | 47.4 | 6.8 | 0.5 | 52.1 | 7.9 | 0.5 | 43.2 | 6.3 | 0.0
Erythema | 1.1 | 0.0 | 0.0 | 1.6 | 0.5 | 0.0 | 1.6 | 0.5 | 0.0
Swelling | 0.5 | 0.0 | 0.0 | 3.2 | 0.5 | 0.0 | 1.1 | 0.0 | 0.0
Induration | 0.5 | 0.0 | 0.0 | 1.6 | 0.5 | 0.0 | 0.5 | 0.0 | 0.0
Ecchymosis | 0.5 | 0.0 | 0.0 | 0.5 | 0.0 | 0.0 | 0.5 | 0.0 | 0.0
Systemic adverse reactions
Myalgia | 23.7 | 5.8 | 0.0 | 25.3 | 5.8 | 0.0 | 16.8 | 5.8 | 0.0
Headache | 15.8 | 3.2 | 0.5 | 18.4 | 6.3 | 0.5 | 18.0 | 4.2 | 0.0
Malaise | 10.5 | 1.6 | 1.1 | 14.7 | 3.2 | 1.1 | 12.1 | 4.7 | 0.5
Shivering | 2.6 | 0.5 | 0.0 | 5.3 | 1.1 | 0.0 | 3.2 | 0.5 | 0.0
Fever (≥100.4°F) [Fever measured by any route] | 0.0 | 0.0 | 0.0 | 0.5 | 0.5 | 0.0 | 0.5 | 0.5 | 0.0

Unsolicited non-serious adverse events were reported in 33 (17.4%) recipients in the Fluzone Quadrivalent group, 45 (23.7%) recipients in the TIV-1 group, and 45 (23.7%) recipients in the TIV-2 group. The most commonly reported unsolicited non-serious adverse events were headache, cough, and oropharyngeal pain. In the follow-up period, there were two SAEs, 1 (0.5%) in the Fluzone Quadrivalent group and 1 (0.5%) in the TIV-2 group.

Geriatric Adults

In Study 4 (NCT01218646), a multi-center, randomized, double-blind trial conducted in the US, adults 65 years of age and older received one dose of either Fluzone Quadrivalent, or one of two formulations of comparator trivalent influenza vaccine (TIV-1 or TIV-2). Each of the trivalent formulations contained an influenza type B virus that corresponded to one of the two type B viruses in Fluzone Quadrivalent (a type B virus of the Victoria lineage or a type B virus of the Yamagata lineage). The safety analysis set included 675 recipients. Among participants in the three vaccine groups combined, 55.7% were female (Fluzone Quadrivalent, 57.3%; TIV-1, 56.0%; TIV-2, 53.8%), 89.5% Caucasian (Fluzone Quadrivalent, 87.6%; TIV-1, 89.8%; TIV-2, 91.1%), 2.2% Black (Fluzone Quadrivalent, 4.0%; TIV-1, 1.8%; TIV-2, 0.9%), 7.4% Hispanic (Fluzone Quadrivalent, 8.4%; TIV-1, 7.6%; TIV-2, 6.2%) and 0.9% were of other racial/ethnic groups (Fluzone Quadrivalent, 0.0%; TIV-1, 0.9%; TIV-2, 1.8%).

Table 6 summarizes solicited injection-site and systemic adverse reactions reported within 7 days post-vaccination via diary cards. Participants were monitored for unsolicited adverse events and SAEs during the 21 days following vaccination.

Table 6: Percentage of Solicited Injection-site and Systemic Adverse Reactions Within 7 Days After Vaccination in Adults 65 Years of Age and Older (Safety Analysis Set) [The safety analysis set includes all persons who received study vaccine] (Study 4 [NCT01218646])
 | Fluzone Quadrivalent [Fluzone Quadrivalent containing A/California/07/2009 (H1N1), A/Victoria/210/2009 (H3N2), B/Brisbane/60/2008 (Victoria lineage), and B/Florida/04/2006 (Yamagata lineage)] (N [N is the number of participants in the safety analysis set] =225) |  |  | TIV-1 [2010-2011 Fluzone TIV containing A/California/07/2009 (H1N1), A/Victoria/210/2009 (H3N2), and B/Brisbane/60/2008 (Victoria lineage), licensed] (B Victoria) (N=225) |  |  | TIV-2 [Investigational TIV containing A/California/07/2009 (H1N1), A/Victoria/210/2009 (H3N2), and B/Florida/04/2006 (Yamagata lineage), non-licensed] (B Yamagata) (N=225)
 | Any (%) | Grade 2 [Grade 2 - Injection-site pain: some interference with activity; Injection-site erythema and Injection-site swelling: ≥5.1 to ≤10 cm; Fever: ≥101.2°F to ≤102.0°F; Myalgia, Headache, and Malaise: some interference with activity] (%) | Grade 3 [Grade 3 - Injection-site pain: Significant; prevents daily activity; Injection-site erythema and Injection-site swelling: >10 cm; Fever: ≥102.1°F; Myalgia, Headache, and Malaise: Significant; prevents daily activity] (%) | Any (%) | Grade 2 (%) | Grade 3 (%) | Any (%) | Grade 2 (%) | Grade 3 (%)
Injection-site adverse reactions
Pain | 32.6 | 1.3 | 0.9 | 28.6 | 2.7 | 0.0 | 23.1 | 0.9 | 0.0
Erythema | 2.7 | 0.9 | 0.0 | 1.3 | 0.0 | 0.0 | 1.3 | 0.4 | 0.0
Swelling | 1.8 | 0.4 | 0.0 | 1.3 | 0.0 | 0.0 | 0.0 | 0.0 | 0.0
Systemic adverse reactions
Myalgia | 18.3 | 4.0 | 0.4 | 18.3 | 4.0 | 0.0 | 14.2 | 2.7 | 0.4
Headache | 13.4 | 1.3 | 0.4 | 11.6 | 1.3 | 0.0 | 11.6 | 1.8 | 0.4
Malaise | 10.7 | 4.5 | 0.4 | 6.3 | 0.4 | 0.0 | 11.6 | 2.7 | 0.9
Fever (≥100.4°F) [Fever measured by any route] | 1.3 | 0.0 | 0.4 | 0.0 | 0.0 | 0.0 | 0.9 | 0.4 | 0.4

Unsolicited non-serious adverse events were reported in 28 (12.4%) recipients in the Fluzone Quadrivalent group, 22 (9.8%) recipients in the TIV-1 group, and 22 (9.8%) recipients in the TIV-2 group. The most commonly reported adverse events were oropharyngeal pain, rhinorrhea, injection-site induration, and headache. Three SAEs were reported during the follow-up period, 2 (0.9%) in the TIV-1 group and 1 (0.4%) in the TIV-2 group.

6.2 Post-Marketing Experience

The following events have been spontaneously reported during the post-approval use of Fluzone or Fluzone Quadrivalent. Because these events are reported voluntarily from a population of uncertain size, it is not always possible to reliably estimate their frequency or establish a causal relationship to vaccine exposure. Adverse events were included based on one or more of the following factors: severity, frequency of reporting, or strength of evidence for a causal relationship to Fluzone or Fluzone Quadrivalent.

- Blood and Lymphatic System Disorders: Thrombocytopenia, lymphadenopathy
- Immune System Disorders: Anaphylaxis, other allergic/hypersensitivity reactions (including urticaria, angioedema)
- Eye Disorders: Ocular hyperemia
- Nervous System Disorders: Guillain Barré syndrome (GBS), convulsions, febrile convulsions, myelitis (including encephalomyelitis and transverse myelitis), facial palsy (Bell's palsy), optic neuritis/neuropathy, brachial neuritis, syncope (shortly after vaccination), dizziness, paresthesia
- Vascular Disorders: Vasculitis, vasodilatation/flushing
- Respiratory, Thoracic and Mediastinal Disorders: Dyspnea, cough, wheezing, throat tightness, oropharyngeal pain, rhinorrhea
- Skin and Subcutaneous Tissue Disorders: Rash, pruritus, and Stevens-Johnson syndrome
- General Disorders and Administration Site Conditions: Asthenia/fatigue, pain in extremities, chest pain
- Gastrointestinal Disorders: Vomiting

8 USE IN SPECIFIC POPULATIONS

8.1 Pregnancy

Risk Summary

All pregnancies have a risk of birth defect, loss, or other adverse outcomes. In the U.S. general population, the estimated background risk of major birth defects and miscarriage in clinically recognized pregnancies is 2% to 4% and 15% to 20%, respectively.

Available data with Fluzone Quadrivalent use in pregnant women are insufficient to inform vaccine-associated risk of adverse developmental outcomes.

A developmental toxicity study was performed in female rabbits administered Fluzone Quadrivalent prior to mating and during gestation. The dose was 0.5 mL on each of five occasions (a single human dose is 0.5 mL). This study revealed no adverse effects to the fetus or pre-weaning development and no evidence of impaired female fertility due to Fluzone Quadrivalent (see Data).

Data

Animal Data: A developmental toxicity study was performed in female rabbits administered a Fluzone Quadrivalent by intramuscular injection on 24 and 10 days before insemination, and on Days 6, 12, and 27 of gestation. The dose was 0.5 mL on each occasion (a single human dose is 0.5 mL). This study revealed no vaccine related fetal malformations and no adverse effects on pre-weaning development or female fertility.

Clinical Considerations

Disease-associated Maternal and/or Embryo/Fetal Risk

Pregnant women are at increased risk of complications associated with influenza infection compared to non-pregnant women. Pregnant women who contract influenza may be at increased risk for adverse pregnancy outcomes, including preterm labor and delivery.

8.2 Lactation

Risk Summary

It is not known whether Fluzone Quadrivalent is excreted in human milk. Data are not available to assess the effects of Fluzone Quadrivalent on the breastfed infant or on milk production/excretion.

The developmental and health benefits of breastfeeding should be considered along with the mother's clinical need for Fluzone Quadrivalent and any potential adverse effects on the breastfed child from Fluzone Quadrivalent or from the underlying maternal condition. For preventive vaccines, the underlying maternal condition is susceptibility to the disease prevented by the vaccine.

8.4 Pediatric Use

Safety and effectiveness of Fluzone Quadrivalent in children below the age of 6 months have not been established. Safety and effectiveness of Fluzone Quadrivalent in children 9 through 17 years of age is based on safety and effectiveness in children 6 months through 8 years of age and adults 18 years of age and older.

8.5 Geriatric Use

Safety and immunogenicity of Fluzone Quadrivalent were evaluated in adults 65 years of age and older. [See Clinical Studies (14.6).] Antibody responses to Fluzone Quadrivalent are lower in persons ≥65 years of age than in younger adults.

11 DESCRIPTION

Fluzone Quadrivalent (Influenza Vaccine) for intramuscular use is an inactivated influenza vaccine, prepared from influenza viruses propagated in embryonated chicken eggs. The virus-containing allantoic fluid is harvested and inactivated with formaldehyde. Influenza virus is concentrated and purified in a linear sucrose density gradient solution using a continuous flow centrifuge. The virus is then chemically disrupted using a non-ionic surfactant, octylphenol ethoxylate (Triton® X-100), producing a "split virus". The split virus containing hemagglutinin (HA) antigen is further purified and then suspended in sodium phosphate-buffered isotonic sodium chloride solution. The Fluzone Quadrivalent process uses an additional concentration factor after the ultrafiltration step in order to obtain a higher hemagglutinin (HA) antigen concentration. The purified split virus from the four strains included in the vaccine are produced separately and then combined to make the quadrivalent formulation.

Fluzone Quadrivalent is an injectable suspension and is clear and slightly opalescent in color.

Antibiotics are not used in the manufacture of Fluzone Quadrivalent.

The Fluzone Quadrivalent prefilled syringe and multi-dose vial presentations are not made with natural rubber latex.

Fluzone Quadrivalent is standardized according to United States Public Health Service requirements and is formulated to contain HA of each of the following four influenza strains recommended for the 2025–2026 influenza season: A/Victoria/4897/2022 IVR-238 (H1N1), A/Croatia/10136RV/2023 X-425A (H3N2), B/Phuket/3073/2013 (B Yamagata lineage), and B/Michigan/01/2021 (a B/Austria/1359417/2021-like virus, B Victoria lineage).

The amounts of HA and other ingredients per dose of vaccine are listed in Table 7. The 0.5 mL single-dose, pre-filled syringe presentation is manufactured and formulated without thimerosal or any other preservative. The 5 mL multi-dose vial presentation contains thimerosal, a mercury derivative, added as a preservative. Each 0.5 mL dose from the multi-dose vial contains 25 mcg mercury. Each 0.25 mL dose from the multi-dose vial contains 12.5 mcg mercury.

Table 7: Fluzone Quadrivalent Ingredients
Ingredient | Quantity (per dose)
Ingredient | Fluzone Quadrivalent 0.25 mL Dose | Fluzone Quadrivalent 0.5 mL Dose
Active Substance: Split influenza virus, inactivated strains [per United States Public Health Service (USPHS) requirement] : | 30 mcg HA total | 60 mcg HA total
A (H1N1) | 7.5 mcg HA | 15 mcg HA
A (H3N2) | 7.5 mcg HA | 15 mcg HA
B/(Victoria lineage) | 7.5 mcg HA | 15 mcg HA
B/(Yamagata lineage) | 7.5 mcg HA | 15 mcg HA
Other:
Sodium phosphate-buffered isotonic sodium chloride solution | QS [Quantity Sufficient] to appropriate volume | QS to appropriate volume
Formaldehyde | ≤50 mcg | ≤100 mcg
Octylphenol ethoxylate | ≤125 mcg | ≤250 mcg
Preservative
Single-dose presentation | - | -
Multi-dose presentation (thimerosal) | 12.5 mcg mercury | 25 mcg mercury
"-" Indicates information is not applicable

12 CLINICAL PHARMACOLOGY

12.1 Mechanism of Action

Specific levels of hemagglutination inhibition (HI) antibody titer post-vaccination with inactivated influenza virus vaccines have not been correlated with protection from influenza virus infection. In some human studies, antibody titers ≥1:40 have been associated with protection from influenza illness in up to 50% of participants. (2) (3)

Antibodies against one influenza virus type or subtype confer limited or no protection against another. Furthermore, antibodies to one antigenic variant of influenza virus might not protect against a new antigenic variant of the same type or subtype. Frequent development of antigenic variants through antigenic drift is the virologic basis for seasonal epidemics and the reason for the usual change of one or more new strains in each year's influenza vaccine.

13 NONCLINICAL TOXICOLOGY

13.1 Carcinogenesis, Mutagenesis, Impairment of Fertility

Fluzone Quadrivalent has not been evaluated for carcinogenic or mutagenic potential, or for impairment of fertility in males.

14 CLINICAL STUDIES

The effectiveness of Fluzone Quadrivalent was demonstrated based on clinical endpoint efficacy data for Fluzone (trivalent influenza vaccine) and on an evaluation of serum HI antibody responses to Fluzone Quadrivalent. Fluzone Quadrivalent, an inactivated influenza vaccine that contains the hemagglutinins of two influenza A subtype viruses and two influenza type B viruses, is manufactured according to the same process as Fluzone.

14.1 Efficacy of Fluzone (Trivalent Influenza Vaccine) in Children 6 through 24 Months of Age

Study 5 (NCT not available), a randomized, double-blind, placebo-controlled study was conducted at a single US center during the 1999-2000 (Year 1) and 2000-2001 (Year 2) influenza seasons. The intent-to-treat analysis set included a total of 786 children 6 through 24 months of age. Participants received two 0.25 mL doses of either Fluzone (N = 525) or a placebo (N = 261). Among all randomized participants in both years, the mean age was 13.8 months; 52.5% were male, 50.8% were Caucasian, 42.0% were Black, and 7.2% were of other racial groups. Cases of influenza were identified through active and passive surveillance for influenza-like illness or acute otitis media and confirmed by culture. Influenza-like illness was defined as fever with signs or symptoms of an upper respiratory infection. Vaccine efficacy against all influenza viral types and subtypes was a secondary endpoint and is presented in Table 8.

Table 8: Estimated Efficacy of Fluzone (Trivalent Influenza Vaccine) Against Culture-Confirmed Influenza in Children Aged 6 through 24 Months during the 1999-2000 and 2000-2001 Influenza Seasons – Intent-to-Treat Analysis Set [The intent-to-treat analysis set includes all enrolled participants who were randomly assigned to receive Fluzone or placebo and vaccinated] (Study 5)
 | Fluzone [Fluzone (0.25 mL): 1999-2000 formulation containing A/Beijing/262/95 (H1N1), A/Sydney/15/97 (H3N2), and B/Yamanashi/166/98 (Yamagata lineage) and 2000-2001 formulation containing A/New Caledonia/20/99 (H1N1), A/Panama/2007/99 (H3N2), and B/Yamanashi/166/98 (Yamagata lineage)] |  |  |  | Placebo [Placebo: 0.4% NaCl] |  |  |  | Fluzone vs. Placebo
Year | n [n is the number of participants with culture-confirmed influenza for the given year of study as listed in the first column] | N [N is the number of participants randomly assigned to receive Fluzone or placebo for the given year of study as listed in the column headers (intent-to-treat analysis set)] | Rate (n/N) [Rate (%) = (n/N) * 100] | (95% CI) | n | N | Rate (n/N) | (95% CI) | Relative Risk (95% CI) | Percent Relative Reduction [Relative reduction in vaccine efficacy was defined as (1-relative risk) × 100] (95% CI)
Year 1 [Includes all culture confirmed influenza cases throughout the study duration for Year 1 (12 months of follow-up)] (1999-2000) | 15 | 273 | 5.5 | (3.1; 8.9) | 22 | 138 | 15.9 | (10.3; 23.1) | 0.34 (0.18; 0.64) | 66 (36; 82)
Year 2 [Includes all culture-confirmed influenza cases throughout the study duration for Year 2 (6 months of follow-up)] (2000-2001) | 9 | 252 | 3.6 | (1.6; 6.7) | 4 | 123 | 3.3 | (0.9; 8.1) | 1.10 (0.34; 3.50) | -10 (-250; 66)

14.2 Efficacy of Fluzone (Trivalent Influenza Vaccine) in Adults

Study 6 (NCT00538512), a randomized, double-blind, placebo-controlled study was conducted in a single US center during the 2007-2008 influenza season. Participants received one dose of either Fluzone vaccine (N = 813), an active comparator (N = 814), or placebo (N = 325). The intent-to-treat analysis set included 1138 healthy adults who received Fluzone or placebo. Participants were 18 through 49 years of age (mean age was 23.3 years); 63.3% were female, 83.1% were Caucasian, and 16.9% were of other racial/ethnic groups. Cases of influenza were identified through active and passive surveillance and confirmed by cell culture and/or real-time polymerase chain reaction (PCR). Influenza-like illness was defined as an illness with at least 1 respiratory symptom (cough or nasal congestion) and at least 1 constitutional symptom (fever or feverishness, chills, or body aches). Vaccine efficacy of Fluzone against all influenza viral types and subtypes is presented in Table 9.

Table 9: Estimated Efficacy of Fluzone (Trivalent Influenza Vaccine) Against Influenza in Adults Aged 18 through 49 Years during the 2007-2008 Influenza Season – Intent-to-Treat Analysis Set [The intent-to-treat analysis set includes all enrolled participants who were randomly assigned to receive Fluzone or placebo and vaccinated] (Study 6 [NCT00538512])
Laboratory-Confirmed Symptomatic Influenza | Fluzone [Fluzone: 2007-2008 formulation containing A/Solomon Islands/3/2006 (H1N1), A/Wisconsin/67/2005 (H3N2), and B/Malaysia/2506/2004 (Victoria lineage)] (N=813) [N is the number of participants randomly assigned to receive Fluzone or placebo] |  |  | Placebo [Placebo: 0.9% NaCl] (N=325) |  |  | Fluzone vs. Placebo
 | n [n is the number of participants satisfying the criteria listed in the first column] | Rate (%) [Rate (%) = (n/N) * 100] | (95% CI) | n | Rate (%) | (95% CI) | Relative Risk (95% CI) | Percent Relative Reduction [Relative reduction in vaccine efficacy was defined as (1 - relative risk) × 100] (95% CI)
Positive culture | 21 | 2.6 | (1.6; 3.9) | 31 | 9.5 | (6.6; 13.3) | 0.27 (0.16; 0.46) | 73 (54; 84)
Positive PCR | 28 | 3.4 | (2.3; 4.9) | 35 | 10.8 | (7.6; 14.7) | 0.32 (0.20; 0.52) | 68 (48; 80)
Positive culture, positive PCR, or both | 28 | 3.4 | (2.3; 4.9) | 35 | 10.8 | (7.6; 14.7) | 0.32 (0.20; 0.52) | 68 (48; 80)

14.3 Immunogenicity of Fluzone Quadrivalent in Children 6 Months through 8 Years of Age

In Study 1 (NCT01240746) [see Adverse Reactions (6.1)], 1419 children 6 months through 35 months of age and 2101 children 3 years through 8 years of age were included in the per-protocol immunogenicity analysis. Participants 6 months through 35 months of age received one or two 0.25 mL doses and participants 3 years through 8 years of age received one or two 0.5 mL doses of Fluzone Quadrivalent, TIV-1, or TIV-2. For participants who received two doses, the doses were administered approximately 4 weeks apart. The distribution of demographic characteristics was similar to that of the safety analysis set [see Adverse Reactions (6.1)].

HI antibody geometric mean titers (GMTs) and seroconversion rates 28 days following vaccination with Fluzone Quadrivalent were non-inferior to those following each TIV for all four strains, based on pre-specified criteria (see Table 10 and Table 11).

Table 10: Non-inferiority of Fluzone Quadrivalent Relative to TIV for Each Strain by HI Antibody GMTs at 28 Days Post-Vaccination, Persons 6 Months Through 8 Years of Age [Participants 6-35 months old received 1 or 2 doses (0.25 mL) and participants 3-8 years old received 1 or 2 doses (0.5 mL) as per ACIP recommendation] (Per-protocol Analysis Set) [Per-protocol analysis set included all persons who had no study protocol deviations] (Study 1 [NCT01240746])
Antigen Strain | Fluzone Quadrivalent [Fluzone Quadrivalent containing A/California/07/2009 (H1N1), A/Victoria/210/2009 (H3N2), B/Brisbane/60/2008 (Victoria lineage), and B/Florida/04/2006 (Yamagata lineage)] N [N is the number of participants in the per-protocol analysis set] =2339 | Pooled TIV [Pooled TIV group includes participants vaccinated with either TIV-1 or TIV-2] N=1181 |  | GMT Ratio (95% CI) [Non-inferiority was demonstrated if the lower limit of the 2-sided 95% CI of the ratio of GMTs (Fluzone Quadrivalent divided by pooled TIV for the A strains, or the TIV containing the corresponding B strain) was >0.66]
 | GMT | GMT
A (H1N1) | 1124 | 1096 |  | 1.03 (0.93; 1.14)
A (H3N2) | 822 | 828 |  | 0.99 (0.91; 1.08)
 | Fluzone Quadrivalent N=2339 | TIV-1 [2010-2011 Fluzone TIV containing A/California/07/2009 (H1N1), A/Victoria/210/2009 (H3N2), and B/Brisbane/60/2008 (Victoria lineage), licensed] (B Victoria) N=582 | TIV-2 [Investigational TIV containing A/California/07/2009 (H1N1), A/Victoria/210/2009 (H3N2), and B/Florida/04/2006 (Yamagata lineage), non-licensed] (B Yamagata) N=599 | GMT Ratio (95% CI)
 | GMT | GMT | GMT
B/Brisbane/60/2008 (B Victoria) | 86.1 | 64.3 | (19.5) [TIV-2 did not contain B/Brisbane/60/2008] | 1.34 (1.20; 1.50)
B/Florida/04/2006 (B Yamagata) | 61.5 | (16.3) [TIV-1 did not contain B/Florida/60/2006] | 58.3 | 1.06 (0.94; 1.18)

Table 11: Non-inferiority of Fluzone Quadrivalent Relative to TIV for Each Strain by Seroconversion Rates at 28 Days Post-Vaccination, Persons 6 Months Through 8 Years of Age [Participants 6-35 months old received 1 or 2 doses (0.25 mL) and participants 3-8 years old received 1 or 2 doses (0.5 mL) as per ACIP recommendations] (Per-protocol Analysis Set) [Per-protocol analysis set included all persons who had no study protocol deviations] (Study 1 [NCT01240746])
Antigen Strain | Fluzone Quadrivalent [Fluzone Quadrivalent containing A/California/07/2009 (H1N1), A/Victoria/210/2009 (H3N2), B/Brisbane/60/2008 (Victoria lineage), and B/Florida/04/2006 (Yamagata lineage)] N [N is the number of participants in the per-protocol analysis set] =2339 | Pooled TIV [Pooled TIV group includes participants vaccinated with either TIV-1 or TIV-2] N=1181 |  | Difference of Seroconversion Rates (95% CI) [Non-inferiority was demonstrated if the lower limit of the 2-sided 95% CI of the difference in seroconversion rates (Fluzone Quadrivalent minus pooled TIV for the A strains, or the TIV containing the corresponding B strain) was >-10%]
 | Seroconversion [Seroconversion: Paired samples with pre-vaccination HI titer <1:10 and post-vaccination titer ≥1:40 or a minimum 4-fold increase for participants with pre-vaccination titer ≥1:10] (%) |  |  | Difference of Seroconversion Rates (95% CI) [Non-inferiority was demonstrated if the lower limit of the 2-sided 95% CI of the difference in seroconversion rates (Fluzone Quadrivalent minus pooled TIV for the A strains, or the TIV containing the corresponding B strain) was >-10%]
A (H1N1) | 92.4 | 91.4 |  | 0.9 (-0.9; 3.0)
A (H3N2) | 88.0 | 84.2 |  | 3.8 (1.4; 6.3)
 | Fluzone Quadrivalent N=2339 | TIV-1 [2010-2011 Fluzone TIV containing A/California/07/2009 (H1N1), A/Victoria/210/2009 (H3N2), and B/Brisbane/60/2008 (Victoria lineage), licensed] (B Victoria) N=582 | TIV-2 [Investigational TIV containing A/California/07/2009 (H1N1), A/Victoria/210/2009 (H3N2), and B/Florida/04/2006 (Yamagata lineage), non-licensed] (B Yamagata) N=599 | Difference of Seroconversion Rates (95% CI)
 | Seroconversion (%) |  |  | Difference of Seroconversion Rates (95% CI)
B/Brisbane/60/2008 (B Victoria) | 71.8 | 61.1 | (20.0) [TIV-2 did not contain B/Brisbane/60/2008] | 10.7 (6.4; 15.1)
B/Florida/04/2006 (B Yamagata) | 66.1 | (17.9) [TIV-1 did not contain B/Florida/04/2006] | 64.0 | 2.0 (-2.2; 6.4)

Non-inferiority immunogenicity criteria based on HI antibody GMTs and seroconversion rates were also met when age subgroups (6 months to <36 months and 3 years to <9 years) were examined. In addition, HI antibody GMTs and seroconversion rates following Fluzone Quadrivalent were higher than those following TIV for the B strain not contained in each respective TIV based on pre-specified criteria (the lower limit of the 2-sided 95% CI of the ratio of the GMTs [Fluzone Quadrivalent divided by TIV] >1.5 for each B strain in Fluzone Quadrivalent compared with the corresponding B strain not contained in each TIV and the lower limit of the two 2-sided 95% CI of the difference of the seroconversion rates [Fluzone Quadrivalent minus TIV] >10% for each B strain in Fluzone Quadrivalent compared with the corresponding B strain not contained in each TIV).

14.4 Immunogenicity of the 0.5 mL Dose of Fluzone Quadrivalent in Children 6 Months through 35 Months of Age

In Study 2 (NCT02915302) [see Adverse Reactions (6.1)], 1027 children, 6 months through 35 months of age, were included in the per-protocol immunogenicity analysis. The distribution of demographic characteristics was similar to that of the safety analysis set [see Adverse Reactions (6.1)].

In this study, children 6 months through 35 months of age received one or two doses of either 0.25 mL or 0.5 mL of Fluzone Quadrivalent. Non-inferiority of the 0.5 mL dose(s) relative to the 0.25 mL dose(s) of Fluzone Quadrivalent was demonstrated for all four strains based on pre-specified criteria (lower limit of the 2-sided 95% CI of the ratio of GMTs between groups >0.667; lower limit of the 2-sided 95% CI of the difference in seroconversion rates >-10%). GMT ratios (GMT0.5-mL dose divided by GMT0.25-mL dose) for the A/H1N1, A/H3N2, B Victoria lineage, and B Yamagata lineage strains were 1.42 (95% CI: 1.16; 1.74), 1.48 (95% CI: 1.21; 1.82), 1.33 (95% CI: 1.09; 1.62), and 1.41 (95% CI: 1.17; 1.70), respectively. Seroconversion rate (SCR) differences (SCR0.5-mL dose minus SCR0.25-mL dose) for the A/H1N1, A/H3N2, B Victoria lineage, and B Yamagata lineage strains were 4.6% (95% CI: -0.4%; 9.6%), 5.1% (95% CI: 0.4%; 9.8%), 1.3% (95% CI: -2.9%; 5.6%), and 2.6% (95% CI: -1.4%; 6.5%).

14.5 Immunogenicity of Fluzone Quadrivalent in Adults ≥18 Years of Age

In Study 3 (NCT00988143) [see Adverse Reactions (6.1)], 565 adults 18 years of age and older who had received one dose of Fluzone Quadrivalent, TIV-1, or TIV-2 were included in the per-protocol immunogenicity analysis. The distribution of demographic characteristics was similar to that of the safety analysis set [see Adverse Reactions (6.1)].

HI antibody GMTs 21 days following vaccination with Fluzone Quadrivalent were non-inferior to those following each TIV for all four strains, based on pre-specified criteria (see Table 12).

Table 12: Non-inferiority of Fluzone Quadrivalent Relative to TIV for Each Strain by HI Antibody GMTs at 21 Days Post-Vaccination, Adults 18 Years of Age and Older (Per-protocol Analysis Set) [Per-protocol analysis set included all persons who had no study protocol deviations] (Study 3 [NCT00988143])
Antigen Strain | Fluzone Quadrivalent [Fluzone Quadrivalent containing A/Brisbane/59/2007 (H1N1), A/Uruguay/716/2007 (H3N2), B/Brisbane/60/2008 (Victoria lineage), and B/Florida/04/2006 (Yamagata lineage)] N [N is the number of participants in the per-protocol analysis set] =190 | Pooled TIV [Pooled TIV group includes participants vaccinated with either TIV-1 or TIV-2] N=375 |  | GMT Ratio (95% CI) [Non-inferiority was demonstrated if the lower limit of the 2-sided 95% CI of the ratio of GMTs (Fluzone Quadrivalent divided by pooled TIV for the A strains, or the TIV containing the corresponding B strain) was >2/3]
 | GMT | GMT |  | GMT Ratio (95% CI) [Non-inferiority was demonstrated if the lower limit of the 2-sided 95% CI of the ratio of GMTs (Fluzone Quadrivalent divided by pooled TIV for the A strains, or the TIV containing the corresponding B strain) was >2/3]
A (H1N1) | 161 | 151 |  | 1.06 (0.87; 1.31)
A (H3N2) | 304 | 339 |  | 0.90 (0.70; 1.15)
 | Fluzone Quadrivalent N=190 | TIV-1 [2009-2010 Fluzone TIV containing A/Brisbane/59/2007 (H1N1), A/Uruguay/716/2007 (H3N2), and B/Brisbane/60/2008 (Victoria lineage), licensed] (B Victoria) N=187 | TIV-2 [2008-2009 Fluzone TIV containing A/Brisbane/59/2007 (H1N1), A/Uruguay/716/2007 (H3N2), and B/Florida/04/2006 (Yamagata lineage), licensed] (B Yamagata) N=188 | GMT Ratio (95% CI)
 | GMT | GMT | GMT | GMT Ratio (95% CI)
B/Brisbane/60/2008 (B Victoria) | 101 | 114 | (44.0) [TIV-2 did not contain B/Brisbane/60/2008] | 0.89 (0.70; 1.12)
B/Florida/04/2006 (B Yamagata) | 155 | (78.1) [TIV-1 did not contain B/Florida/04/2006] | 135 | 1.15 (0.93; 1.42)

14.6 Immunogenicity of Fluzone Quadrivalent in Geriatric Adults ≥65 Years of Age

In Study 4 (NCT01218646) [see Adverse Reactions (6.1)], 660 adults 65 years of age and older were included in the per-protocol immunogenicity analysis. The distribution of demographic characteristics was similar to that of the safety analysis set [see Adverse Reactions (6.1)].

HI antibody GMTs 21 days following vaccination with Fluzone Quadrivalent were non-inferior to those following TIV for all four strains, based on pre-specified criteria (see Table 13).

Seroconversion rates 21 days following Fluzone Quadrivalent were non-inferior to those following TIV for H3N2, B/Brisbane, and B/Florida, but not for H1N1 (see Table 14). The HI antibody GMT following Fluzone Quadrivalent was higher than that following TIV-1 for B/Florida but not higher than that following TIV-2 for B/Brisbane, based on pre-specified criteria (the lower limit of the 2-sided 95% CI of the ratio of the GMTs [Fluzone Quadrivalent divided by TIV] >1.5 for each B strain in Fluzone Quadrivalent compared with the corresponding B strain not contained in each TIV). Seroconversion rates following Fluzone Quadrivalent were higher than those following TIV for the B strain not contained in each respective TIV, based on pre-specified criteria (the lower limit of the two 2-sided 95% CI of the difference of the seroconversion rates [Fluzone Quadrivalent minus TIV] >10% for each B strain in Fluzone Quadrivalent compared with the corresponding B strain not contained in each TIV).

Table 13: Non-inferiority of Fluzone Quadrivalent Relative to TIV for Each Strain by HI Antibody GMTs at 21 Days Post-Vaccination, Adults 65 Years of Age and Older (Per-protocol Analysis Set) [Per-protocol analysis set included all persons who had no study protocol deviations] (Study 4 [NCT01218646])
Antigen Strain | Fluzone Quadrivalent [Fluzone Quadrivalent containing A/California/07/2009 (H1N1), A/Victoria/210/2009 (H3N2), B/Brisbane/60/2008 (Victoria lineage), and B/Florida/04/2006 (Yamagata lineage)] N [N is the number of participants in the per-protocol analysis set] =220 | Pooled TIV [Pooled TIV group includes participants vaccinated with either TIV-1 or TIV-2] N=440 |  | GMT Ratio (95% CI) [Non-inferiority was demonstrated if the lower limit of the 2-sided 95% CI of the ratio of GMTs (Fluzone Quadrivalent divided by pooled TIV for the A strains, or the TIV containing the corresponding B strain) was >0.66]
 | GMT | GMT |  | GMT Ratio (95% CI) [Non-inferiority was demonstrated if the lower limit of the 2-sided 95% CI of the ratio of GMTs (Fluzone Quadrivalent divided by pooled TIV for the A strains, or the TIV containing the corresponding B strain) was >0.66]
A (H1N1) | 231 | 270 |  | 0.85 (0.67; 1.09)
A (H3N2) | 501 | 324 |  | 1.55 (1.25; 1.92)
 | Fluzone Quadrivalent N=220 | TIV-1 [2010-2011 Fluzone TIV containing A/California/07/2009 (H1N1), A/Victoria/210/2009 (H3N2), and B/Brisbane/60/2008 (Victoria lineage), licensed] (B Victoria) N=219 | TIV-2 [Investigational TIV containing A/California/07/2009 (H1N1), A/Victoria/210/2009 (H3N2), and B/Florida/04/2006 (Yamagata lineage), non-licensed] (B Yamagata) N=221 | GMT Ratio (95% CI)
 | GMT | GMT | GMT | GMT Ratio (95% CI)
B/Brisbane/60/2008 (B Victoria) | 73.8 | 57.9 | (42.2) [TIV-2 did not contain B/Brisbane/60/2008] | 1.27 (1.05; 1.55)
B/Florida/04/2006 (B Yamagata) | 61.1 | (28.5) [TIV-1 did not contain B/Florida/04/2006] | 54.8 | 1.11 (0.90; 1.37)

Table 14: Non-inferiority of Fluzone Quadrivalent Relative to TIV for Each Strain by Seroconversion Rates at 21 Days Post-Vaccination, Adults 65 Years of Age and Older (Per-protocol Analysis Set) [Per-protocol analysis set included all persons who had no study protocol deviations] (Study 4 [NCT01218646])
Antigen Strain | Fluzone Quadrivalent [Fluzone Quadrivalent containing A/California/07/2009 (H1N1), A/Victoria/210/2009 (H3N2), B/Brisbane/60/2008 (Victoria lineage), and B/Florida/04/2006 (Yamagata lineage)] N [N is the number of participants in the per-protocol analysis set] =220 | Pooled TIV [Pooled TIV group includes participants vaccinated with either TIV-1 or TIV-2] N=440 |  | Difference of Seroconversion Rates (95% CI) [Non-inferiority was demonstrated if the lower limit of the 2-sided 95% CI of the difference in seroconversion rates (Fluzone Quadrivalent minus pooled TIV for the A strains, or the TIV containing the corresponding B strain) was >-10%]
 | Seroconversion [Seroconversion: Paired samples with pre-vaccination HI titer <1:10 and post-vaccination titer ≥1:40 or a minimum 4-fold increase for participants with pre-vaccination titer ≥1:10] (%) |  |  | Difference of Seroconversion Rates (95% CI) [Non-inferiority was demonstrated if the lower limit of the 2-sided 95% CI of the difference in seroconversion rates (Fluzone Quadrivalent minus pooled TIV for the A strains, or the TIV containing the corresponding B strain) was >-10%]
A (H1N1) | 65.91 | 69.77 |  | -3.86 (-11.50; 3.56)
A (H3N2) | 69.09 | 59.32 |  | 9.77 (1.96; 17.20)
 | Fluzone Quadrivalent N=220 | TIV-1 [2010-2011 Fluzone TIV containing A/California/07/2009 (H1N1), A/Victoria/210/2009 (H3N2), and B/Brisbane/60/2008 (Victoria lineage), licensed] (B Victoria) N=219 | TIV-2 [Investigational TIV containing A/California/07/2009 (H1N1), A/Victoria/210/2009 (H3N2), and B/Florida/04/2006 (Yamagata lineage), non-licensed] (B Yamagata) N=221 | Difference of Seroconversion Rates (95% CI)
 | Seroconversion(%) |  |  | Difference of Seroconversion Rates (95% CI)
B/Brisbane/60/2008 (B Victoria) | 28.64 | 18.72 | (8.60) [TIV-2 did not contain B/Brisbane/60/2008] | 9.91 (1.96; 17.70)
B/Florida/04/2006 (B Yamagata) | 33.18 | (9.13) [TIV-1 did not contain B/Florida/04/2006] | 31.22 | 1.96 (-6.73; 10.60)

15 REFERENCES

1 Lasky T, Terracciano GJ, Magder L, et al. The Guillain-Barré syndrome and the 1992-1993 and 1993-1994 influenza vaccines. N Engl J Med 1998;339:1797-802.
2 Hannoun C, Megas F, Piercy J. Immunogenicity and protective efficacy of influenza vaccination. Virus Res 2004;103:133-138.
3 Hobson D, Curry RL, Beare AS, Ward-Gardner A. The role of serum haemagglutination-inhibiting antibody in protection against challenge infection with influenza A2 and B viruses. J Hyg Camb 1972;70:767-777.

16 HOW SUPPLIED/STORAGE AND HANDLING

16.1 How Supplied

Single-dose, prefilled syringe (clear plunger rod), without needle, 0.5 mL (NDC 49281-926-88) (not made with natural rubber latex). Supplied as package of 10 (NDC 49281-926-50).

Multi-dose vial, 5 mL (NDC 49281-541-78) (not made with natural rubber latex). Supplied as package of one (NDC 49281-541-15). A maximum of ten doses can be withdrawn from the multi-dose vial.

16.2 Storage and Handling

Store all Fluzone Quadrivalent presentations refrigerated at 2° to 8°C (35° to 46°F). DO NOT FREEZE. Discard if vaccine has been frozen.

Between uses, return the multi-dose vial to the recommended storage conditions at 2° to 8°C (35° to 46°F).

Do not use after the expiration date shown on the label.

17 PATIENT COUNSELING INFORMATION

See FDA-approved patient labeling (Patient Information). Inform the vaccine recipient or guardian:

- Fluzone Quadrivalent contains killed viruses and cannot cause influenza.
- Fluzone Quadrivalent stimulates the immune system to produce antibodies that help protect against influenza, but does not prevent other respiratory infections.
- Annual influenza vaccination is recommended.
- Report adverse reactions to their healthcare provider and/or to the Vaccine Adverse Event Reporting System (VAERS) at 1-800-822-7967.

Vaccine Information Statements must be provided to vaccine recipients or their guardians, as required by the National Childhood Vaccine Injury Act of 1986 prior to immunization. These materials are available free of charge at the Centers for Disease Control and Prevention (CDC) website (www.cdc.gov/vaccines).

Fluzone is a registered trademark of Sanofi Pasteur Inc.

Manufactured by:
Sanofi Pasteur Inc.
Swiftwater, PA 18370 USA

This product's labeling may have been updated. For the most recent prescribing information, please visit https://dailymed.nlm.nih.gov/dailymed/.

Patient Information Sheet

Fluzone® Quadrivalent
Influenza Vaccine

Please read this information sheet before getting Fluzone Quadrivalent. This summary is not intended to take the place of talking with your healthcare provider. If you have questions or would like more information, please talk with your healthcare provider.

What is Fluzone Quadrivalent?

Fluzone Quadrivalent is a vaccine that helps protect against influenza illness (flu).

Fluzone Quadrivalent is for people who are 6 months of age and older.

Vaccination with Fluzone Quadrivalent may not protect all people who receive the vaccine.

Who should not get Fluzone Quadrivalent?

You should not get Fluzone Quadrivalent if you:

- ever had a severe allergic reaction to eggs or egg products.
- ever had a severe allergic reaction after getting any influenza vaccine.
- are younger than 6 months of age.

Tell your healthcare provider if you or your child have or have had:

- Guillain-Barré syndrome (severe muscle weakness) after getting an influenza vaccine.
- problems with your immune system as the immune response may be diminished.

How is the Fluzone Quadrivalent given?

Fluzone Quadrivalent is given as an injection into the muscle.

What are the possible side effects of Fluzone Quadrivalent?

The most common side effects of Fluzone Quadrivalent are:

- pain, redness, and swelling where you got the injection
- muscle aches
- tiredness
- headache
- fever

These are not all of the possible side effects of Fluzone Quadrivalent. You can ask your healthcare provider about other side effects.

Call your healthcare provider for advice about any side effects that concern you. You may report side effects to the Vaccine Adverse Event Reporting System (VAERS) at 1-800-822-7967 or http://vaers.hhs.gov.

What are the ingredients in Fluzone Quadrivalent?

Fluzone Quadrivalent contains 4 killed influenza virus strains.

Other ingredients include formaldehyde and octylphenol ethoxylate. The preservative thimerosal is only in the multi-dose vial of Fluzone Quadrivalent.

Manufactured by:
Sanofi Pasteur Inc.
Swiftwater, PA 18370 USA

PRINCIPAL DISPLAY PANEL - 5 mL Vial Label

NDC 49281-541-78

5 mL Multi-Dose Vial

Influenza Vaccine
Fluzone® Quadrivalent

Rx only

2025-2026 Formula
Contains Preservative. DO NOT FREEZE. Store at 2° to 8°C (35° to 46°F).
SHAKE WELL. Contents: One 5 mL multi-dose vial.
0.25 mL or 0.5 mL dose for 6 – 35 months.
0.5 mL dose for 3 years of age and older.
For Intramuscular Use. See package insert for details.
US Govt License #1725

Mfg by: Sanofi Pasteur Inc.

PRINCIPAL DISPLAY PANEL - 5 mL Vial Carton

NDC 49281-541-15

2025-2026
Formula

Influenza Vaccine
Fluzone® Quadrivalent

Rx only

For 6 months of age and older.
For Intramuscular Use.
5 mL multi-dose vial.
0.25 mL or 0.5 mL dose for 6 – 35 months.
0.5 mL dose for 3 years of age and older.

sanofi

PRINCIPAL DISPLAY PANEL - 0.5 mL Syringe Label

NDC 49281-926-88

Influenza Vaccine
Fluzone® Quadrivalent
2025-2026 Formula
Rx only
0.5 mL Single-Dose
No Preservative
For IM Use
Mfd by: Sanofi Pasteur Inc.

PRINCIPAL DISPLAY PANEL - 0.5 mL Syringe Carton

NDC 49281-926-50

2025-2026
Formula

Influenza Vaccine
Fluzone® Quadrivalent

Rx only

For Intramuscular Use
For 6 months of age and older
10 single-dose prefilled syringes 0.5 mL each

sanofi